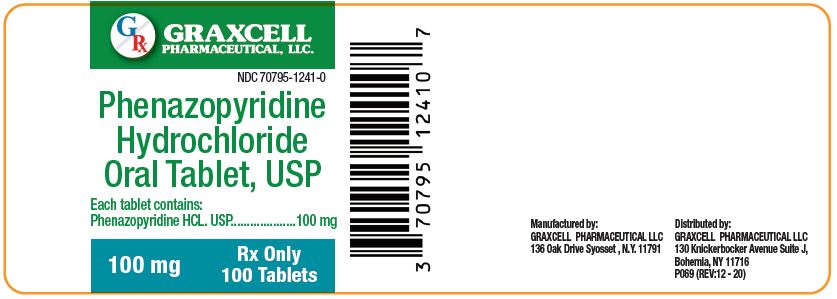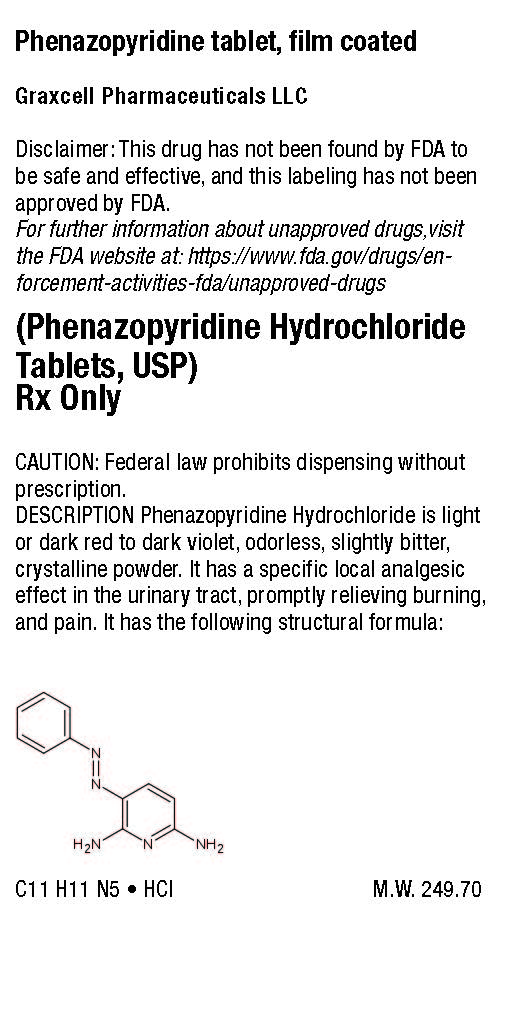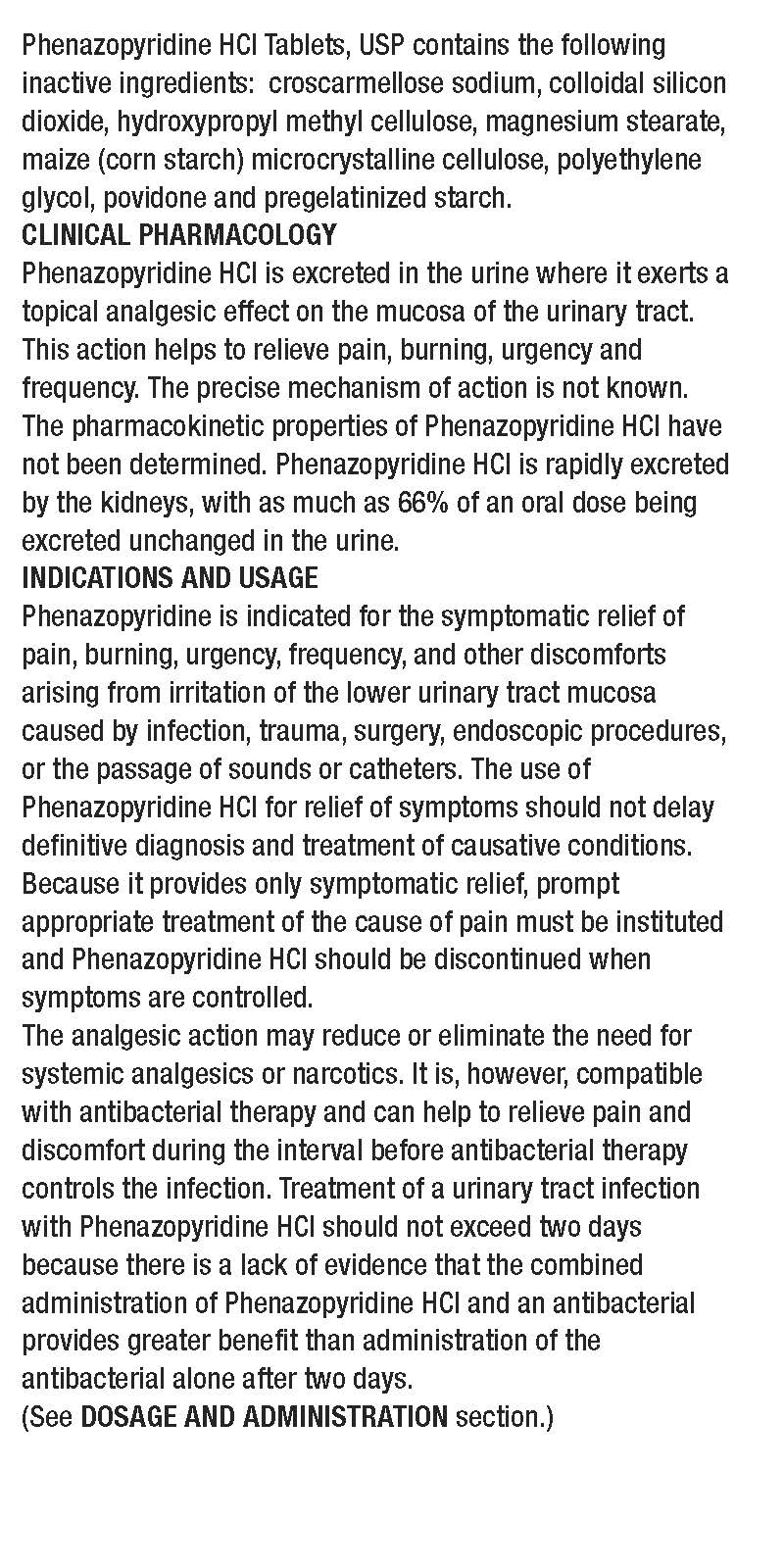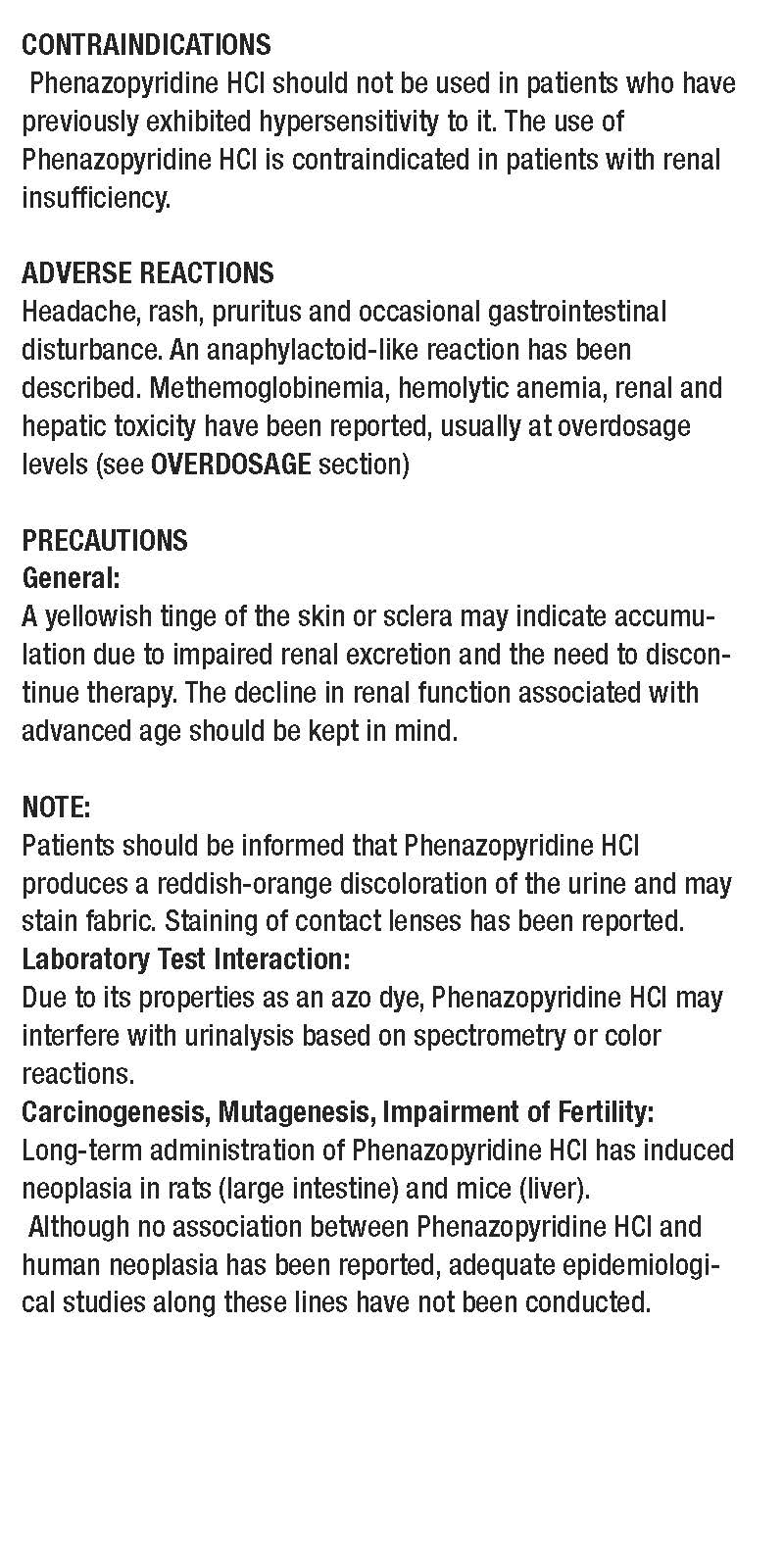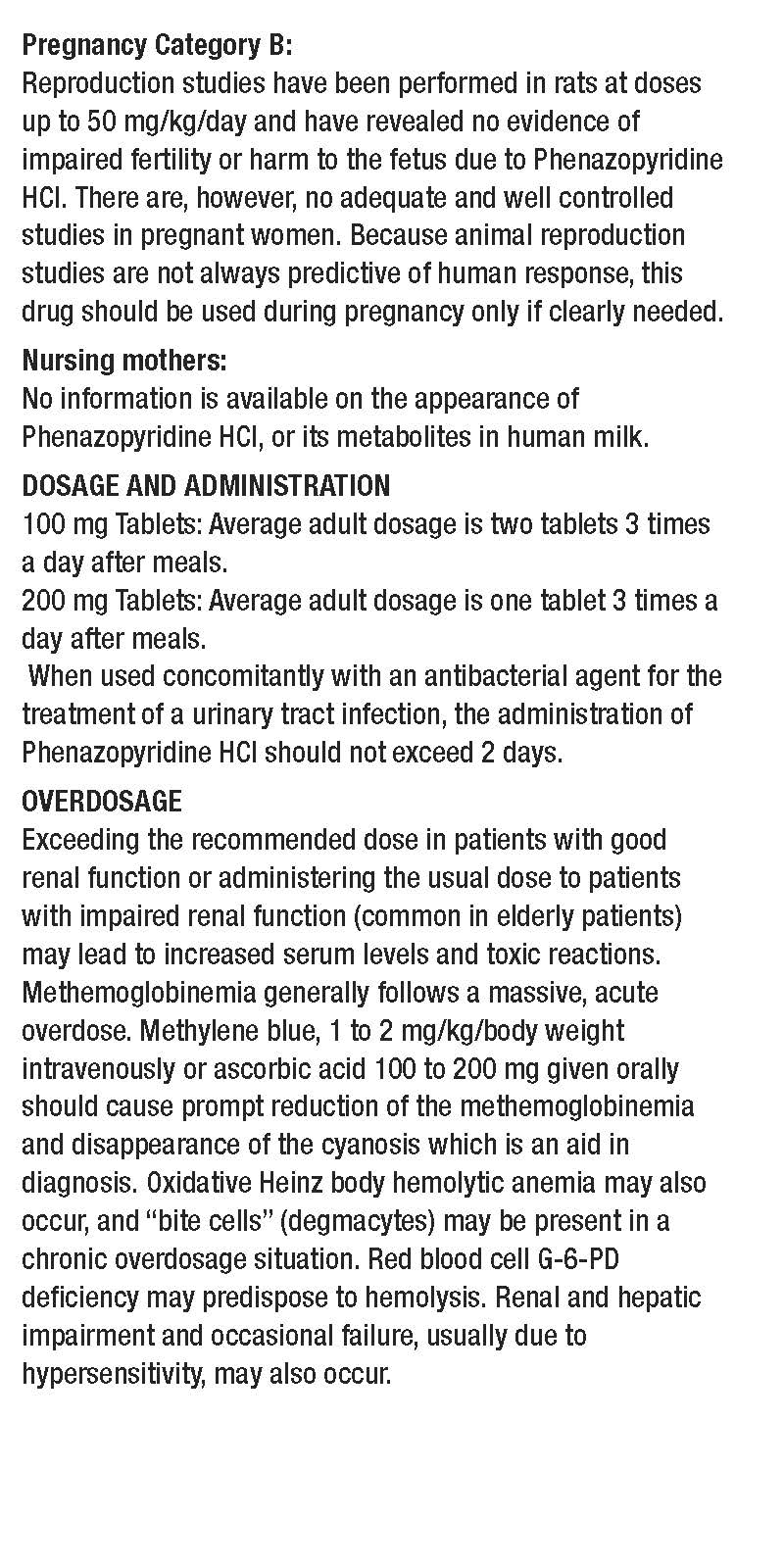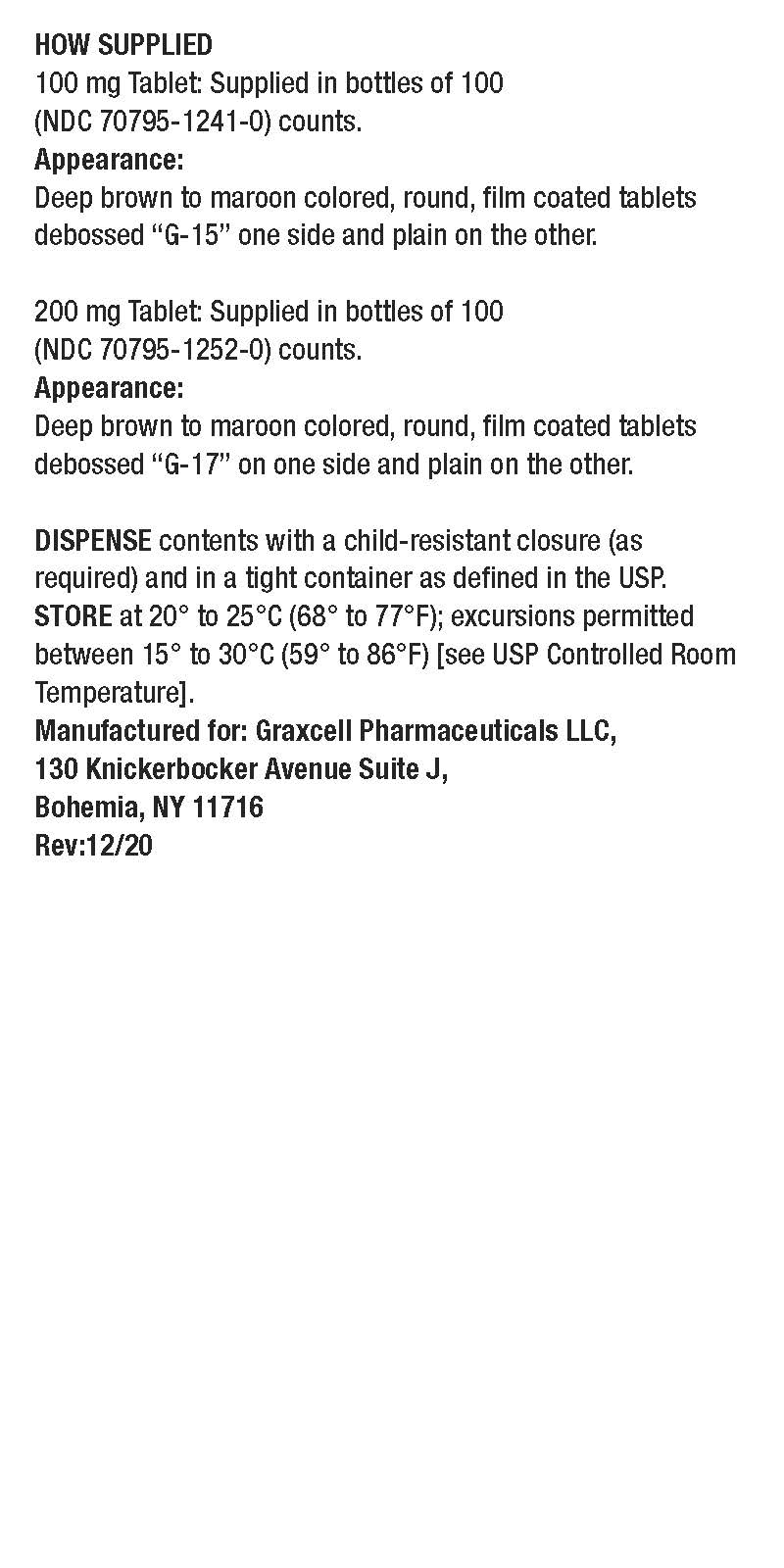 DRUG LABEL: Phenazopyridine Hydrochloride

NDC: 70795-1241 | Form: TABLET
Manufacturer: GRAXCELL PHARMACEUTICAL, LLC
Category: prescription | Type: HUMAN PRESCRIPTION DRUG LABEL
Date: 20211221

ACTIVE INGREDIENTS: PHENAZOPYRIDINE HYDROCHLORIDE 100 mg/1 1
INACTIVE INGREDIENTS: CROSCARMELLOSE SODIUM; SILICON DIOXIDE; HYPROMELLOSE, UNSPECIFIED; MAGNESIUM STEARATE; STARCH, CORN; MICROCRYSTALLINE CELLULOSE; POLYETHYLENE GLYCOL, UNSPECIFIED; POVIDONE

Phenazopyridine Hydrochloride tablet, film coated - 100 mg, 70795-1241

INDICATIONS AND USAGE

Phenazopyridine is indicated for the symptomatic relief of pain, burning, urgency, frequency, and other discomforts arising from irritation of the lower urinary tract mucosa caused by infection, trauma, surgery, endoscopic procedures, or the passage of sounds or catheters. The use of
Phenazopyridine HCl for relief of symptoms should not delay definitive diagnosis and treatment of causative conditions. Because it provides only symptomatic relief, prompt appropriate treatment of the cause of pain must be instituted and Phenazopyridine HCl should be discontinued when
symptoms are controlled. The analgesic action may reduce or eliminate the need for systemic analgesics or narcotics. It is, however, compatible
with antibacterial therapy and can help to relieve pain and discomfort during the interval before antibacterial therapy controls the infection. Treatment of a urinary tract infection with Phenazopyridine HCl should not exceed two days because there is a lack of evidence that the combined administration of Phenazopyridine HCl and an antibacterial provides greater benefit than administration of the antibacterial alone after two days. (See DOSAGE AND ADMINISTRATION section.)

DOSAGE AND ADMINISTRATION

100 mg Tablets: Average adult dosage is two tablets 3 times a day after meals.
When used concomitantly with an antibacterial agent for the treatment of a urinary tract infection, the administration of Phenazopyridine HCl should not exceed 2 days.

INACTIVE INGREDIENTS

Phenazopyridine HCl Tablets, USP contains the following inactive ingredients: croscarmellose sodium, colloidal silicon dioxide, hydroxypropyl methyl cellulose, magnesium stearate, maize (corn starch) microcrystalline cellulose, polyethylene glycol, povidone and pregelatinized starch.